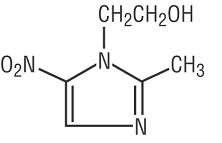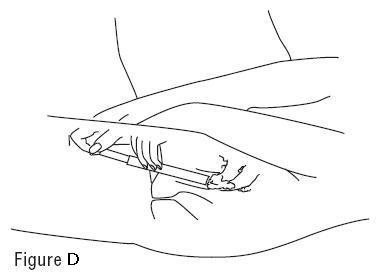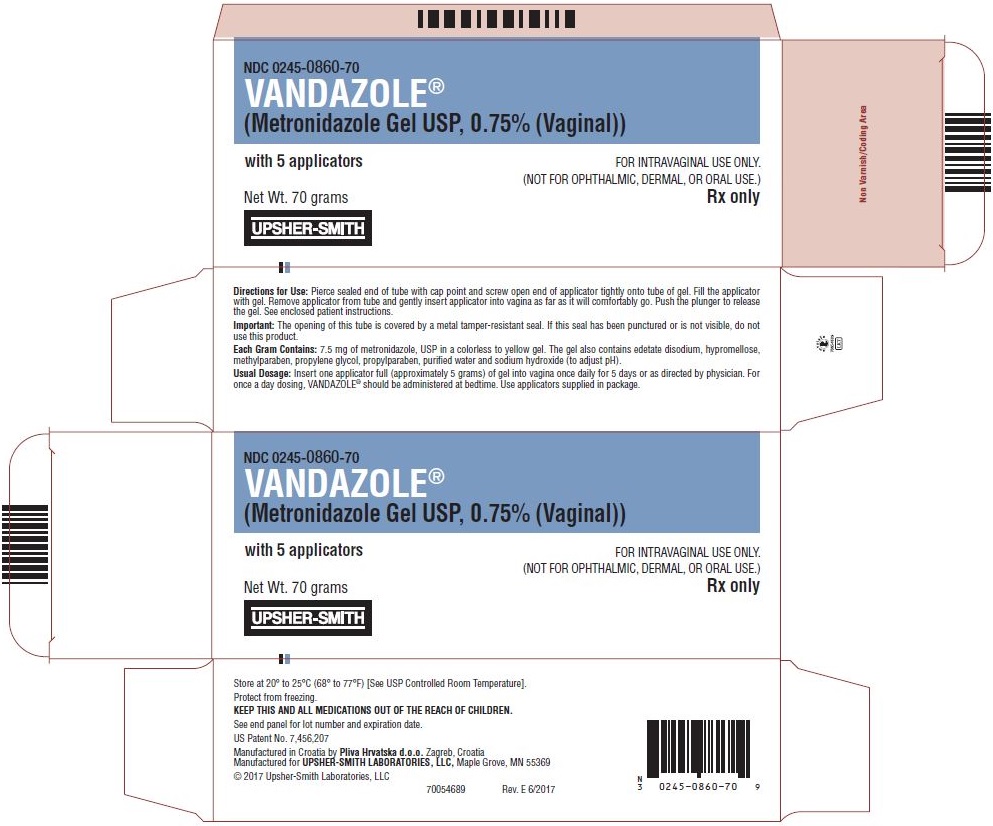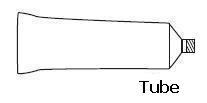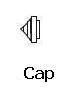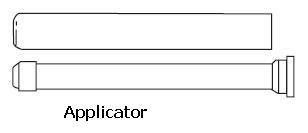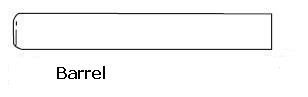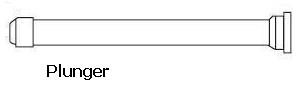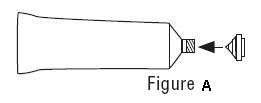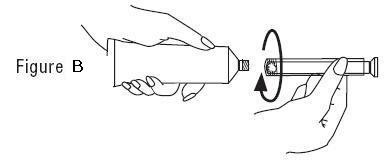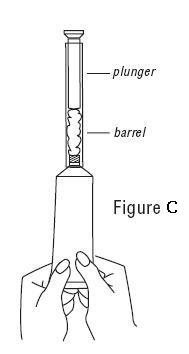 DRUG LABEL: Vandazole
NDC: 0245-0860 | Form: GEL
Manufacturer: Upsher-smith Laboratories, LLC
Category: prescription | Type: HUMAN PRESCRIPTION DRUG LABEL
Date: 20251202

ACTIVE INGREDIENTS: METRONIDAZOLE 7.5 mg/1 g
INACTIVE INGREDIENTS: EDETATE DISODIUM; HYPROMELLOSE, UNSPECIFIED; METHYLPARABEN; PROPYLENE GLYCOL; PROPYLPARABEN; WATER; SODIUM HYDROXIDE

HIGHLIGHTS OF PRESCRIBING INFORMATION

These highlights do not include all the information needed to use VANDAZOLE®safely and effectively. See full prescribing information for VANDAZOLE.
VANDAZOLE®(metronidazole gel), for intravaginal use
Initial U.S. Approval: 1963

RECENT MAJOR CHANGES

Indications and Usage (1) 2/2021

1 INDICATIONS AND USAGE

VANDAZOLE is a nitroimidazole antimicrobial indicated for the treatment of bacterial vaginosis in post-menarchal females. (1)

2 DOSAGE AND ADMINISTRATION

- One applicator full of VANDAZOLE administered intravaginally once a day for 5 days. (2)
- Not for ophthalmic, dermal, or oral use. (2)

3 DOSAGE FORMS AND STRENGTHS

Vaginal gel 0.75% in a 70 g tube with 5 vaginal applicators (each applicator delivers approximately 5 g of gel containing 37.5 mg of metronidazole) (3).

4 CONTRAINDICATIONS

History of hypersensitivity to metronidazole, other nitroimidazole derivatives or parabens (4)

- Disulfiram: Psychotic reactions have been reported with disulfiram and oral metronidazole; do not administer concurrently with or within the last 2 weeks of disulfiram (4.2, 7.1).
- Alcohol: Disulfiram-like reactions to alcohol have been reported with oral metronidazole; do not consume alcohol during and for at least three days following treatment (4.3, 7.2)

5 WARNINGS AND PRECAUTIONS

- Central and Peripheral Nervous System Effects: Convulsive seizures and peripheral neuropathy have been reported in patients treated with oral or intravenous metronidazole; discontinue if abnormal neurologic signs develop. (5.1)
- Carcinogenicity in Animals: Metronidazole has been shown to be carcinogenic in mice and rats. (5.2, 13.1)
- Interference with laboratory tests: Metronidazole may interfere with certain serum chemistry laboratory values (5.3)

6 ADVERSE REACTIONS

Adverse reactions occurring in ≥ 1% of patients are: fungal infection, headache, pruritus, abdominal pain, nausea, dysmenorrhea, pharyngitis, rash, infection, diarrhea, breast pain, and metrorrhagia. (6.1)

To report SUSPECTED ADVERSE REACTIONS, contact Teva Pharmaceuticals USA, Inc. at 1-888-838-2872 or FDA at 1-800-FDA-1088 or www.fda.gov/medwatch.

7 DRUG INTERACTIONS

- Warfarin and other coumarin anticoagulants: Prolonged anticoagulant effects reported with oral metronidazole; monitor INR and prothrombin time. (7.3)
- Lithium: Elevated lithium concentrations reported with oral metronidazole; monitor serum concentrations of lithium. (7.4)

8 USE IN SPECIFIC POPULATIONS

- Lactation: A lactating patient may pump and discard breastmilk during treatment and for 48 hours after the last dose (8.2).

FULL PRESCRIBING INFORMATION

1 INDICATIONS AND USAGE

VANDAZOLE®is indicated in the treatment of bacterial vaginosis (formerly referred to as Haemophilusvaginitis, Gardnerellavaginitis, nonspecific vaginitis, Corynebacteriumvaginitis, or anaerobic vaginosis) in post-menarchal females.

2 DOSAGE AND ADMINISTRATION

The recommended dose is one applicator full of VANDAZOLE, (approximately 5 grams of gel containing approximately 37.5 mg of metronidazole) administered intravaginally once a day for 5 days. For once a day dosing, VANDAZOLE should be administered at bedtime [see Patient Counseling Information (17.4)].

Not for ophthalmic, dermal, or oral use.

3 DOSAGE FORMS AND STRENGTHS

Gel, 0.75%. VANDAZOLE is a clear, colorless to yellow gel in a 70 g tube, supplied with 5 vaginal applicators. Each applicator delivers approximately 5 g of gel containing 37.5 mg of metronidazole, USP.

4 CONTRAINDICATIONS

4.1 Hypersensitivity

The use of VANDAZOLE is contraindicated in patients with a history of hypersensitivity to metronidazole, other nitroimidazole derivatives, or parabens. Reported reactions include urticaria; erythematous rash; Stevens-Johnson Syndrome, toxic epidermal necrolysis, flushing; nasal congestion; dryness of the mouth, vagina, or vulva; fever; pruritus; fleeting joint pains [see Adverse Reactions (6.2)] .

4.2 Psychotic Reaction with Disulfiram

Use of oral metronidazole is associated with psychotic reactions in alcoholic patients who were using disulfiram concurrently. Do not administer VANDAZOLE to patients who have taken disulfiram within the last two weeks [see Adverse Reactions (6.2)] .

4.3 Interaction with Alcohol

Use of oral metronidazole is associated with a disulfiram-like reaction to alcohol, including abdominal cramps, nausea, vomiting, headaches, and flushing [see Adverse Reactions (6.2)] . Discontinue alcohol consumption during and for at least three days after therapy with VANDAZOLE.

5 WARNINGS AND PRECAUTIONS

5.1 Central and Peripheral Nervous System Effects

Use of oral or intravenous metronidazole is associated with convulsive seizures, encephalopathy, aseptic meningitis, optic and peripheral neuropathy, the latter characterized mainly by numbness or paresthesia of an extremity [see Adverse Reactions (6.2)] . VANDAZOLE should be administered with caution to patients with central nervous system diseases. Discontinue VANDAZOLE promptly if a patient develops abnormal neurologic signs.

5.2 Carcinogenicity in Animals

Metronidazole has been shown to be carcinogenic in mice and rats [see Nonclinical Toxicology (13.1)]. Unnecessary use of metronidazole should be avoided. Use of VANDAZOLE should be reserved for the treatment of bacterial vaginosis [see Indications and Usage (1)].

5.3 Interference with Laboratory Tests

Metronidazole may interfere with certain types of determinations of serum chemistry values, such as aspartate aminotransferase (AST, SGOT), alanine aminotransferase (ALT, SGPT), lactate dehydrogenase (LDH), triglycerides, and glucose hexokinase. Values of zero may be observed. All of the assays in which interference has been reported involve enzymatic coupling of the assay to oxidation-reduction of nicotinamide-adenine dinucleotides (NAD + NADH). Interference is due to the similarity in absorbance peaks of NADH (340 nm) and metronidazole (322 nm) at pH 7. Consider postponing chemistry laboratory tests until treatment with VANDAZOLE is completed.

6 ADVERSE REACTIONS

6.1 Clinical Trials Experience

Because clinical trials are conducted under widely varying conditions, adverse reaction rates observed in the clinical trials of a drug cannot be directly compared to rates in the clinical trials of another drug and may not reflect the rates observed in practice.

The data described below reflect exposure to VANDAZOLE compared to another formulation of vaginal metronidazole in 220 women in a single trial. The population was non-pregnant females (age range 18 to 72 years, the mean was 33 years +/- 11 years) with bacterial vaginosis. The racial demographic of those enrolled was 71 (32%) of White, 143 (65%) of Black, 3 (1%) of Hispanic, 2 (1%) of Asian, and 1 (0%) of other. Patients administered an applicator full of VANDAZOLE intravaginally once daily at bedtime for 5 days.

There were no deaths or serious adverse reactions related to drug therapy in the clinical trial. VANDAZOLE was discontinued in 5 patients (2.3%) due to adverse reactions.

The incidence of all adverse reactions in VANDAZOLE-treated patients was 42% (92/220). Adverse reactions occurring in ≥ 1% of patients were: fungal infection* (12%), headache (7%), pruritus (6%), abdominal pain (5%), nausea (3%), dysmenorrhea (3%), pharyngitis (2%), rash (1%), infection (1%), diarrhea (1%), breast pain (1%), and metrorrhagia (1%).

* Known or previously unrecognized vaginal candidiasis may present more prominent symptoms during therapy with VANDAZOLE. Approximately 10% of patients treated with VANDAZOLE developed Candidavaginitis during or immediately after therapy.

Additional uncommon events, reported by < 1% of those women treated with VANDAZOLE included:

General: | allergic reaction, back pain, flu syndrome, mucous membrane disorder, pain
Gastrointestinal: | anorexia, constipation, dyspepsia, flatulence, gingivitis, vomiting
Nervous System: | depression, dizziness, insomnia
Respiratory System: | asthma, rhinitis
Skin and Appendages: | acne, sweating, urticaria
Urogenital System: | breast enlargement, dysuria, female lactation, labial edema, leucorrhea, menorrhagia, pyelonephritis, salpingitis, urinary frequency, urinary tract infection, vaginitis, vulvovaginal disorder

6.2 Other Metronidazole Formulations

Other Vaginal Formulations

Other reactions that have been reported in association with the use of other formulations of metronidazole vaginal gel include: unusual taste and decreased appetite.

Topical (Dermal) Formulations

Other reactions that have been reported in association with the use of topical (dermal) formulations of metronidazole include skin irritation, transient skin erythema, and mild skin dryness and burning. None of these adverse reactions exceeded an incidence of 2% of patients.

Oral and Parenteral Formulations

The following adverse reactions and altered laboratory tests have been reported with the oral or parenteral use of metronidazole:

Cardiovascular:Flattening of the T-wave may be seen in electrocardiographic tracings.

Nervous System:The most serious adverse reactions reported in patients treated with metronidazole have been convulsive seizures, encephalopathy, aseptic meningitis, optic and peripheral neuropathy, the latter characterized mainly by numbness or paresthesia of an extremity. In addition, patients have reported syncope, vertigo, incoordination, ataxia, confusion, dysarthria, irritability, depression, weakness, and insomnia [see Warnings and Precautions (5.1)] .

Gastrointestinal:Abdominal discomfort, nausea, vomiting, diarrhea, an unpleasant metallic taste, anorexia, epigastric distress, abdominal cramping, constipation, “furry” tongue, glossitis, stomatitis, pancreatitis, and modification of taste of alcoholic beverages.

Genitourinary:Overgrowth of Candidain the vagina, dyspareunia, decreased libido, proctitis.

Hematopoietic:Reversible neutropenia, reversible thrombocytopenia.

Hypersensitivity Reactions:Urticaria; erythematous rash; Stevens-Johnson Syndrome, toxic epidermal necrolysis, flushing; nasal congestion; dryness of the mouth, vagina, or vulva; fever; pruritus; fleeting joint pains [see Contraindications (4.1)] .

Renal:Dysuria, cystitis, polyuria, incontinence, a sense of pelvic pressure, darkened urine.

7 DRUG INTERACTIONS

The intravaginal administration of a single 5 gram dose of VANDAZOLE results in relatively lower mean systemic exposure to metronidazole that is approximately 2% to 5% of that achieved following a 500 mg oral dose of metronidazole [see Clinical Pharmacology (12.3)] . The following drug interactions were reported for oral metronidazole.

7.1 Disulfiram

Use of oral metronidazole has been associated with psychotic reactions in alcoholic patients who are using disulfiram concurrently. VANDAZOLE should not be used by patients who have taken disulfiram within the last two weeks [see Contraindications (4.2)] .

7.2 Alcoholic Beverages

Use of oral metronidazole has been associated with a disulfiram-like reaction (abdominal cramps, nausea, vomiting, headaches, and flushing) to alcohol. Alcoholic beverages and preparations containing ethanol or propylene glycol should not be consumed during and for at least three days after VANDAZOLE therapy [see Contraindications (4.3)] .

7.3 Coumarin and Other Oral Anticoagulants

Use of oral metronidazole has been reported to potentiate the anticoagulant effect of warfarin and other coumarin anticoagulants, resulting in a prolongation of prothrombin time. This possible drug interaction should be considered when VANDAZOLE is prescribed for patients on this type of anticoagulant therapy. In patients on oral anticoagulants, consider monitoring prothrombin time, international normalized ratio (INR), and other coagulation parameters while on VANDAZOLE.

7.4 Lithium

Short-term use of oral metronidazole has been associated with elevation of serum lithium concentrations and, in a few cases signs of lithium toxicity, in patients stabilized on relatively high doses of lithium. Use VANDAZOLE with caution in patients treated with lithium and consider monitoring lithium serum concentrations while on VANDAZOLE.

7.5 Cimetidine

Use of oral metronidazole with cimetidine may prolong the half-life and decrease plasma clearance of metronidazole. No dose adjustment of VANDAZOLE is necessary.

8 USE IN SPECIFIC POPULATIONS

8.1 Pregnancy

Risk Summary

Available data on metronidazole use in pregnant women from published cohort studies, case-control studies, case series, meta analyses, and case reports over several decades have not established a drug-associated risk of major birth defects, miscarriage, or adverse maternal or fetal outcomes. In animal reproduction studies, no adverse developmental effects were demonstrated when oral metronidazole was administered to mice at doses up to six times the recommended human dose (see Data).

The estimated background risk of major birth defects and miscarriage for the indicated population is unknown. All pregnancies have a background risk of birth defect, loss, or other adverse outcomes. In the U.S. general population, the estimated background risk of major birth defects and miscarriage in clinically recognized pregnancies is 2 to 4% and 15 to 20%, respectively.

Data

Human Data

Published case-control studies, cohort studies, meta analyses, case series, and case reports over several decades have not established a risk with metronidazole use in pregnancy and major birth defects, miscarriage, or adverse maternal or fetal outcomes. Many studies included first trimester exposures. One study showed an increased risk of cleft lip, with or without cleft palate, in infants exposed to metronidazole in-utero; however, these findings were not confirmed. Most studies did not show an increased risk for congenital anomalies or other adverse fetal outcomes following metronidazole exposure during pregnancy. Studies conducted to assess the risk of infant cancer following systemic metronidazole exposure during pregnancy did not show an increased risk; however, the ability of these studies to detect such a signal was limited.

Animal Data

Animal studies have shown that metronidazole crosses the placental barrier and enters the fetal circulation rapidly. Oral metronidazole reproductive toxicity studies have been performed in mice at doses up to six times the recommended human dose based on body surface area comparisons and have revealed no evidence of harm to the fetus. However, in a single small study where the drug was administered intraperitoneally, some intrauterine deaths were observed.

8.2 Lactation

Risk Summary

There are no data on the presence of metronidazole in human milk following intravaginal administration. Metronidazole is present in human milk following oral metronidazole administration at concentrations similar to those found in plasma (see Data).The metronidazole vaginal gel achieves 2% of the mean maximum serum concentration of a 500 mg oral metronidazole dose [see Clinical Pharmacology (12.3)] . The published literature reports no adverse effects in infants exposed through breastmilk to maternal orally administered metronidazole. There are no data on the effects on milk production.

Animal studies have shown the potential for tumorigenicity after oral metronidazole was administered chronically to rats and mice [see Nonclinical Toxicology (13.1)] . The clinical relevance of these findings is unclear. The developmental and health benefits of breastfeeding should be considered along with the mother’s clinical need for VANDAZOLE, and any potential adverse effects on the breastfed child from VANDAZOLE or from the underlying maternal condition. Alternatively, a lactating patient may interrupt breastfeeding and choose to pump and discard breastmilk during treatment with VANDAZOLE and for 48 hours after the last dose and feed her infant previously stored human milk or formula.

Data

In a study of lactating women receiving oral metronidazole 600 mg (n=11) or 1200 mg (n=4) daily, mean maternal plasma concentrations were 5.0 and 12.5 mcg/mL, respectively, within 2 hours following administration; the milk: maternal plasma ratio was approximately 1.

8.4 Pediatric Use

The safety and efficacy of VANDAZOLE in the treatment of bacterial vaginosis in post-menarchal females have been established on the extrapolation of clinical trial data from adult females.

The safety and efficacy of VANDAZOLE in pre-menarchal females have not been established.

8.5 Geriatric Use

Clinical studies with VANDAZOLE did not include sufficient numbers of subjects 65 years of age or older to determine whether they respond differently than younger subjects. Other reported clinical experience in using metronidazole gel, 1% has not identified differences in responses between elderly and younger patients.

10 OVERDOSAGE

There is no human experience with overdosage of metronidazole vaginal gel. Vaginally applied metronidazole gel, 0.75% could be absorbed in sufficient amounts to produce systemic effects [see Warnings and Precautions (5) and Adverse Reactions (6.2)] .

11 DESCRIPTION

VANDAZOLE (metronidazole gel, USP), 0.75% is the vaginal dosage form of the nitroimidazole antimicrobial metronidazole at a concentration of 0.75%. Chemically, metronidazole is a 2-methyl-5-nitroimidazole-1-ethanol.

C6H9N3O3M.W. 171.16

VANDAZOLE is a colorless to yellow gel, containing metronidazole, USP at a concentration of 7.5 mg/g (0.75%). The gel also contains edetate disodium, hypromellose, methylparaben, propylene glycol, propylparaben, purified water, and sodium hydroxide (to adjust pH).

Each applicator full of 5 grams of vaginal gel contains approximately 37.5 mg of metronidazole, USP.

12 CLINICAL PHARMACOLOGY

12.1 Mechanism of Action

Metronidazole is an antibacterial drug [see Clinical Pharmacology, Microbiology (12.4)]

12.3 Pharmacokinetics

Healthy Subjects

Following a single, intravaginal 5 gram dose of metronidazole vaginal gel (equivalent to 37.5 mg of metronidazole) to 38 healthy female subjects, a mean maximum serum metronidazole concentration of 281 ng/mL was reported (range: 134 to 464 ng/mL). The average time to achieve this Cmaxwas 9.5 hours (range: 4 to 17 hours) after dosing with metronidazole vaginal gel. This Cmaxis approximately 2% of the mean maximum serum concentration reported in healthy subjects administered a single, oral 500 mg dose of metronidazole (mean Cmax= 12,785 ng/mL).

The extent of exposure [area under the curve (AUC)] of metronidazole, when administered as a single intravaginal 5 gram dose of metronidazole vaginal gel (equivalent to 37.5 mg of metronidazole), was 5,989 ng•hr/mL (range: 2,797 to 10,515 ng•hr/mL). This AUC0-∞is approximately 5% of the reported AUC of metronidazole following a single oral 500 mg dose of metronidazole approximately 125,000 ng•hr/mL.

Patients with Bacterial Vaginosis

Following single and multiple 5 gram doses of a similar metronidazole vaginal gel product to 4 patients with bacterial vaginosis, a mean maximum serum metronidazole concentration of 214 ng/mL on Day 1 and 294 ng/mL (range: 228 to 349 ng/mL) on Day 5 were reported. Steady state metronidazole serum concentrations following oral dosages of 400 to 500 mg twice a day have been reported to range from 6,000 to 20,000 ng/mL.

12.4 Microbiology

Mechanism of Action

The intracellular targets of action of metronidazole on anaerobes are largely unknown. The 5-nitro group of metronidazole is reduced by metabolically active anaerobes, and studies have demonstrated that the reduced form of the drug interacts with bacterial DNA. However, it is not clear whether interaction with DNA alone is an important component in the bactericidal action of metronidazole on anaerobic organisms.

Activity In Vitro

Metronidazole is an antibacterial agent active in vitroagainst most strains of the following organisms that have been reported to be associated with bacterial vaginosis:

Bacteroidesspp.

Gardnerella vaginalis

Mobiluncusspp.

Peptostreptococcusspp.

Standard methodology for the susceptibility testing of the potential bacterial vaginosis pathogens, Gardnerella vaginalisand Mobiluncusspp., has not been defined. Culture and sensitivity testing of bacteria are not routinely performed to establish the diagnosis of bacterial vaginosis [see Clinical Studies (14)] .

13 NONCLINICAL TOXICOLOGY

13.1 Carcinogenesis, Mutagenesis, Impairment of Fertility

Metronidazole has shown evidence of carcinogenic activity after chronic oral administration in mice and rats. Pulmonary tumors and lymphomas were reported in several oral mouse studies in which mice were dosed at 75 mg/kg and above (about 5 times the clinical human dose based on body surface area comparison). Malignant liver tumors were reported in male mice dosed at doses equivalent to a human dose of 41 mg/kg/day (33 times the recommended clinical dose based on body surface area comparisons). Chronic oral dosing of metronidazole in rats at doses above 150 mg/kg (about 20 times the clinical human dose based on body surface area comparison) has resulted in mammary and hepatic tumors. Two lifetime tumorigenicity studies in hamsters have been performed and reported to be negative. Although no life-time studies were performed to evaluate the carcinogenic potential of VANDAZOLE (metronidazole gel, USP) 0.75%, published data have shown that intravaginal administration of metronidazole to Wistar rats for 5 days, at doses 26 times the recommended human dose based on body surface area comparisons, has resulted in an increased frequency of micronuclei in rat vaginal mucosal cells.

Metronidazole has shown mutagenic activity in a number of in vitro assay systems. In addition, a dose dependent increase in the frequency of micronuclei was observed in mice after intraperitoneal injections. An increase in chromosome aberrations has been reported in one study of patients with Crohn’s disease who were treated with 200 to 1200 mg/day of metronidazole for 1 to 24 months. However, in a second study, no increase in chromosome aberrations was reported in patients with Crohn’s disease who were treated with metronidazole for 8 months.

Fertility studies have been performed in mice up to six times the recommended human oral dose (based on mg/m^2) and have revealed no evidence of impaired fertility. Metronidazole failed to produce any adverse effects on fertility or testicular function in male rats at doses up to 400 mg/kg/day (about 50 times the maximum recommended clinical dose based on body surface area comparisons) for 28 days. However, male rats treated at the same dose for 6 weeks or longer were infertile and showed severe degeneration of the seminiferous epithelium in the testes as well as marked decreases in testicular spermatid counts and epididymal sperm counts. Fertility was restored in most rats after an eight-week, drug-free recovery period.

14 CLINICAL STUDIES

A single, randomized, double-blind, active-controlled clinical trial was conducted to evaluate the efficacy of VANDAZOLE for the treatment of bacterial vaginosis. A clinical diagnosis of bacterial vaginosis was defined by the presence of a homogeneous vaginal discharge that (a) has a pH of greater than 4.5, (b) emits a "fishy" amine odor when mixed with a 10% KOH solution, and (c) contains clue cells on microscopic examination. Gram's stain results consistent with a diagnosis of bacterial vaginosis include (a) markedly reduced or absent Lactobacillusmorphology, (b) predominance of Gardnerellamorphotype, and (c) absent or few white blood cells. Non-pregnant females at least 18 years of age were randomized to receive treatment with either VANDAZOLE or another formulation of metronidazole vaginal gel 0.75% once daily at bedtime for 5 days. The modified intent-to treat population (patients who received study medication and had a Nugent score ≥ 4) consisted of 229 VANDAZOLE patients and 243 patients treated with another vaginal formulation of metronidazole. Therapeutic Cure defined as a clinical cure and Nugent score < 4 was assessed Day 22-31. Table 1 shows the therapeutic, clinical and Nugent score cure rates in this trial. The therapeutic cure rate was 42.8% for the VANDAZOLE group and 30.9% for the comparator group (95% confidence interval about the 11.9% difference in therapeutic cure rate: 2.8% to 21.0%).

Table 1 Efficacy of Vandazole for the Treatment of Bacterial Vaginosis in a Randomized, Double-Blind Active Controlled Study^1
Outcome | Vandazole n = 229 | Active Control n = 243 | Treatment Difference (%) [95% Confidence Interval]
 | % Cure | % Cure
Therapeutic Cure | 42.8 | 30.9 | 11.9 [2.8, 21.0]
Clinical Cure | 52.4 | 45.3 | 7.1 [-2.3, 16.5]
Nugent Score Cure | 52.0 | 41.1 | 10.9 [1.5, 20.3]
^1Modified intent-to-treat population

16 HOW SUPPLIED/STORAGE AND HANDLING

VANDAZOLE (metronidazole gel, USP), 0.75 % is supplied in a 70-gram tube and is packaged with 5 vaginal applicators. (NDC 0245-0860-70)

Store at 20º to 25ºC (68º to 77ºF) [See USP Controlled Room Temperature]. Avoid exposure to extreme heat or cold. Protect from freezing.

17 PATIENT COUNSELING INFORMATION

Advise the patient to read the FDA-approved patient labeling (Instructions for Use).

Interaction with Alcohol

Instruct the patient not to consume alcoholic beverages and preparations containing ethanol or propylene glycol during and for at least 3 days after treatment with VANDAZOLE [see Contraindications (4.3) and Drug Interactions (7.2)] .

Drug Interactions

Instruct the patient not to use VANDAZOLE if disulfiram had been used within the last two weeks [see Contraindications (4.2)], and to inform their healthcare provider if they are taking oral anticoagulants, or lithium [see Drug Interactions (7.3, 7.4)] .

Vaginal Intercourse and Use with Vaginal Products

Instruct the patient not to engage in vaginal intercourse or use other vaginal products (such as tampons or douches) during treatment with VANDAZOLE.

Fungal Vaginal Infections

Inform the patient that vaginal fungal infections can occur following use of VANDAZOLE and may require treatment with an antifungal drug [see Adverse Reactions (6.1)] .

Lactation

A patient may choose to pump and discard breastmilk during treatment with VANDAZOLE and for 48 hours after last dose, and feed her infant previously stored human milk or formula [see Use in Specific Populations (8.2)] .

Accidental Exposure to the Eye

Inform the patient that VANDAZOLE contains ingredients that may cause burning and irritation of the eye. In the event of accidental contact with the eye, rinse the eye with copious amounts of cool tap water and consult a healthcare provider.

Vaginal Irritation

Inform the patient to discontinue use and consult a healthcare provider if vaginal irritation occurs with use of VANDAZOLE.

Administration of Drug

Instruct the patient that VANDAZOLE (metronidazole gel, USP), 0.75% is supplied with 5 vaginal applicators. For once daily dosing, one applicator full should be used per dose.

US Patent No. 7,456,207

Manufactured In Croatia By:
Pliva Hrvatska d.o.o.
Zagreb, Croatia

Manufactured For:
UPSHER-SMITH LABORATORIES, LLC
Maple Grove, MN 55369

Rev. H 2/2021

PATIENT INSTRUCTIONS FOR USE

VANDAZOLE®(van-DA-zole)
(metronidazole gel, USP), 0.75%

For vaginal use only.

Do not put VANDAZOLE in your eyes, mouth, or on your skin.

Read this Patient Instructions for Use before you start using VANDAZOLE. This leaflet does not take the place of talking with your healthcare provider about your medical condition or your treatment.

Instructions for use:

1. Filling the applicator

- Remove the cap and puncture the metal seal on the tube with the pointed tip of the cap. (See Figure A)

- Screw the end of applicator onto the tube. (See Figure B)

- Slowly squeeze the gel out of tube and into the applicator. The plunger will stop when the applicator is full. (See Figure C)

- Unscrew the applicator and replace the cap on the tube.

2. Inserting the applicator

- You can insert the applicator into your vagina:
  - while you lie on your back with your knees bent or
  - in any position that is comfortable for you
- Hold the filled applicator by the barrel, and gently insert into your vagina as far as it will comfortably go. (See Figure D)

- Slowly push the plunger in until all of the gel goes into your vagina (See Figure D).
- Take the empty applicator out of your vagina.

3. Care of the applicator

This product comes with 5 vaginal applicators.

- After use, throw away the empty applicator in the trash.

While you use VANDAZOLE you should not have vaginal intercourse or use other vaginal products (such as tampons or douches).

If vaginal irritation develops when you use VANDAZOLE, discontinue use and consult your healthcare provider.

If you get VANDAZOLE in your eye, rinse your eye with cool tap water and consult a healthcare provider.

How should I store VANDAZOLE?

- Store VANDAZOLE at 68ºF to 77ºF (20ºC to 25ºC).
- Avoid exposure to extreme heat or cold. Avoid freezing VANDAZOLE.
- Keep this and all medicines out of reach of children.

Manufactured In Croatia By:
Pliva Hrvatska d.o.o.
Zagreb, Croatia

Manufactured For:
UPSHER-SMITH LABORATORIES, LLC
Maple Grove, MN 55369

© 2021 Upsher-Smith Laboratories, LLC

Rev. E 2/2021

Package/Label Display Panel

NDC 0245-0860-70

VANDAZOLE®

(Metronidazole Gel USP, 0.75% [Vaginal])

with 5 applicators

FOR INTRAVAGINAL USE ONLY.

(NOT FOR OPHTHAMIC, DERMAL, OR ORAL USE.)

Rx only

Net Wt. 70 grams

UPSHER-SMITH